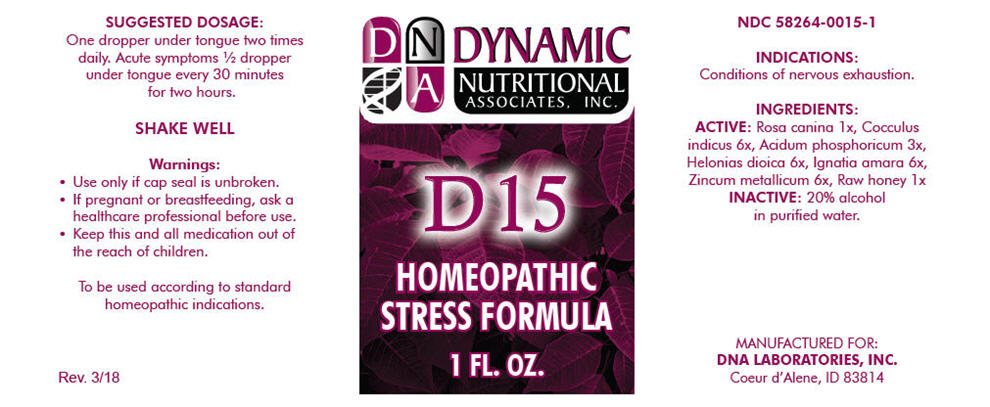 DRUG LABEL: D-15
NDC: 58264-0015 | Form: SOLUTION
Manufacturer: DNA Labs, Inc.
Category: homeopathic | Type: HUMAN OTC DRUG LABEL
Date: 20250113

ACTIVE INGREDIENTS: ROSA CANINA FRUIT 1 [hp_X]/1 mL; ANAMIRTA COCCULUS SEED 6 [hp_X]/1 mL; PHOSPHORIC ACID 3 [hp_X]/1 mL; CHAMAELIRIUM LUTEUM ROOT 6 [hp_X]/1 mL; STRYCHNOS IGNATII SEED 6 [hp_X]/1 mL; ZINC 6 [hp_X]/1 mL; HONEY 1 [hp_X]/1 mL
INACTIVE INGREDIENTS: ALCOHOL; WATER

D-15

NDC 58264-0015-1

INDICATIONS

PURPOSE

Conditions of nervous exhaustion.

INGREDIENTS

ACTIVE

Rosa canina 1x, Cocculus indicus 6x, Acidum phosphoricum 3x, Helonias dioica 6x, Ignatia amara 6x, Zincum metallicum 6x, Raw honey 1x

INACTIVE

20% alcohol in purified water.

SUGGESTED DOSAGE

One dropper under tongue two times daily. Acute symptoms ½ dropper under tongue every 30 minutes for two hours.

STORAGE AND HANDLING

SHAKE WELL

Warnings

- Use only if cap seal is unbroken.

PREGNANCY OR BREAST FEEDING

- If pregnant or breastfeeding, ask a healthcare professional before use.

KEEP OUT OF REACH OF CHILDREN

- Keep this and all medication out of the reach of children.

To be used according to standard homeopathic indications.

PRINCIPAL DISPLAY PANEL - 1 FL. OZ. Bottle Label

DYNAMIC
NUTRITIONAL
ASSOCIATES, INC.

D 15

HOMEOPATHIC
STRESS FORMULA

1 FL. OZ.